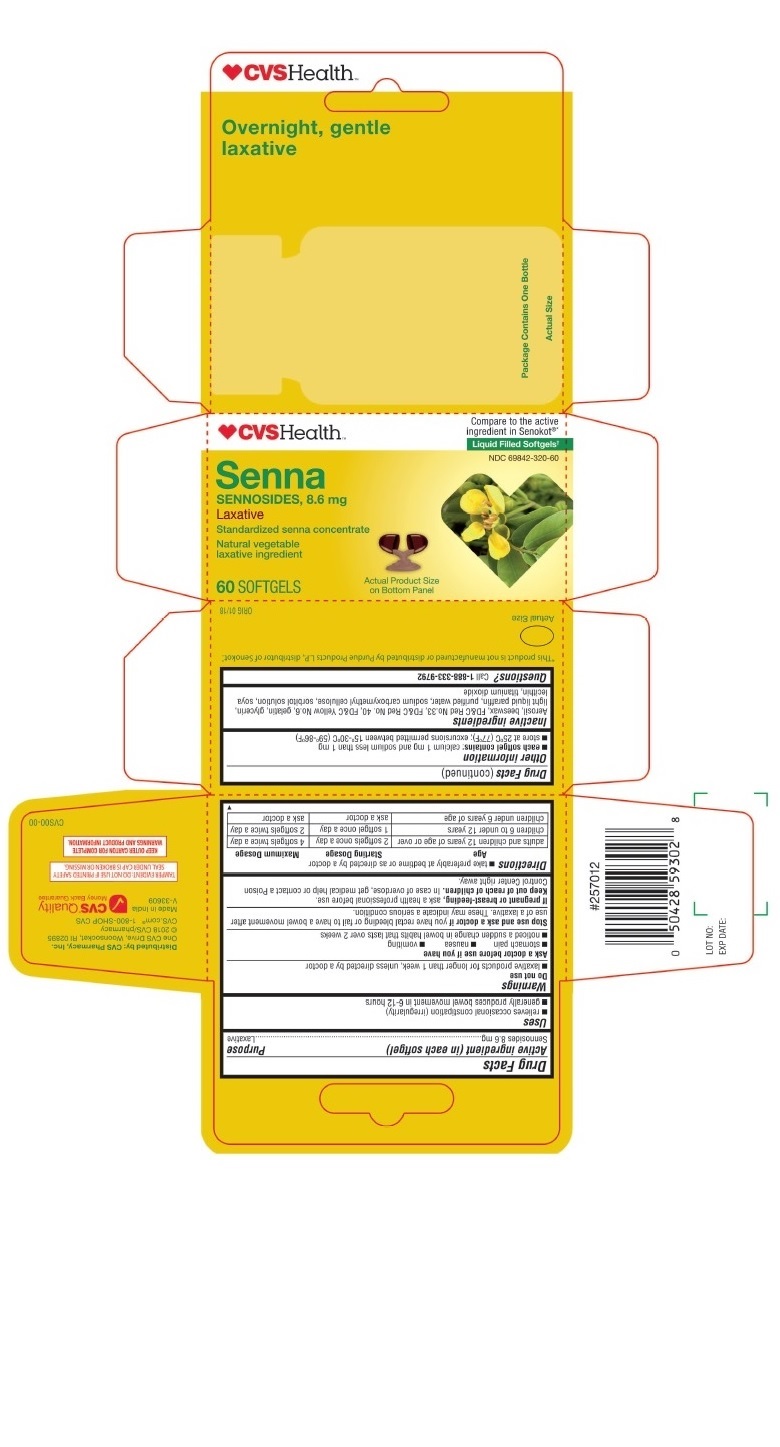 DRUG LABEL: SENNA
NDC: 69842-320 | Form: CAPSULE, GELATIN COATED
Manufacturer: CVS
Category: otc | Type: HUMAN OTC DRUG LABEL
Date: 20241216

ACTIVE INGREDIENTS: SENNOSIDES 8.6 mg/1 1
INACTIVE INGREDIENTS: YELLOW WAX; SILICON DIOXIDE; D&C RED NO. 33; FD&C RED NO. 40; GELATIN; GLYCERIN; MINERAL OIL; WATER; CARBOXYMETHYLCELLULOSE SODIUM; SORBITOL; LECITHIN, SOYBEAN; TITANIUM DIOXIDE

CVS SENNA

Drug Facts

ACTIVE INGREDIENT

Active ingredient (in each softgel) Purpose

Sennosides 8.6 mg..............................................................Laxative

Uses

- relieves occasional constipation (irregularity)
- generally produces bowel movement in 6-12 hours

Warnings

Do not use

- laxative products for longer than 1 week, unless directed by a doctor

Ask a doctor before use if you have

- stomach pain
- nausea
- vomiting
- noticed a sudden change in bowel habits that lasts over 2 weeks

Stop use and ask a doctor if

- you have rectal bleeding or fail to have a bowel movement after use of a laxative. These may indicate a serious condition.

PREGNANCY OR BREAST FEEDING

If pregnant or breast-feeding, ask a health professional before use.

Keep out of reach of children. In case of overdose, get medical help or contact a Poison Control Center right away.

Directions

- take preferably at bedtime or as directed by a doctor

Age | Starting Dosage | Maximum Dosage
adults and children 12 years of age or older | 2 softgels once a day | 4 softgels twice a day
children 6 to under 12 years | 1 softgel once a day | 2 softgels twice a day
children under 6 years of age | ask a doctor | ask a doctor

Other information

- each softgel contains: calcium 1 mg and sodim less than 1 mg
- store at 25°C (77°F); excursions permitted between 15°-30°C (59°-86°F)

Inactive ingredients

Aerosil, beeswax, FD&C Red No. 33, FD&C Yellow No.6, gelatin, glycerin, light liquid paraffin, purified water, sodium carboxymethyl cellulose, sorbitol solution, soya lecithin, titanium dioxide

Questions?

Call 1-888-333-9792

Distributed by: CVS Pharmacy, Inc.
One CVS Drive, Woonsocket, RI 02895

PRINCIPAL DISPLAY PANEL - CVS SENNA 60 Softgels Bottle Carton

♥CVSHealth™

Compare to the active
ingredient in Senokot®*

Liquid Filled Softgels†

NDC 69842-320-60

Senna
SENNOSIDES, 8.6 mg
Laxative

Standardized senna concentrate

Natural vegetable

laxative ingredient

60 SOFTGELS

Actual Product Size

on Bottom Panel